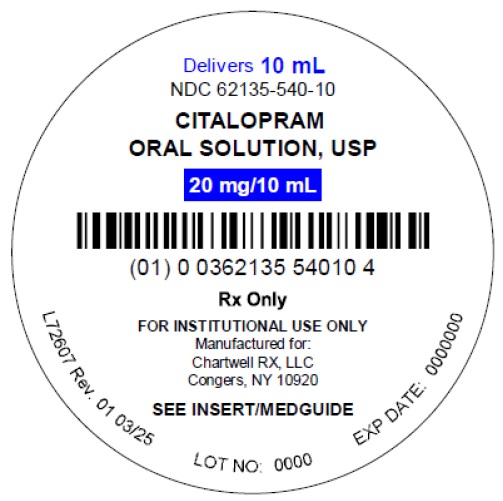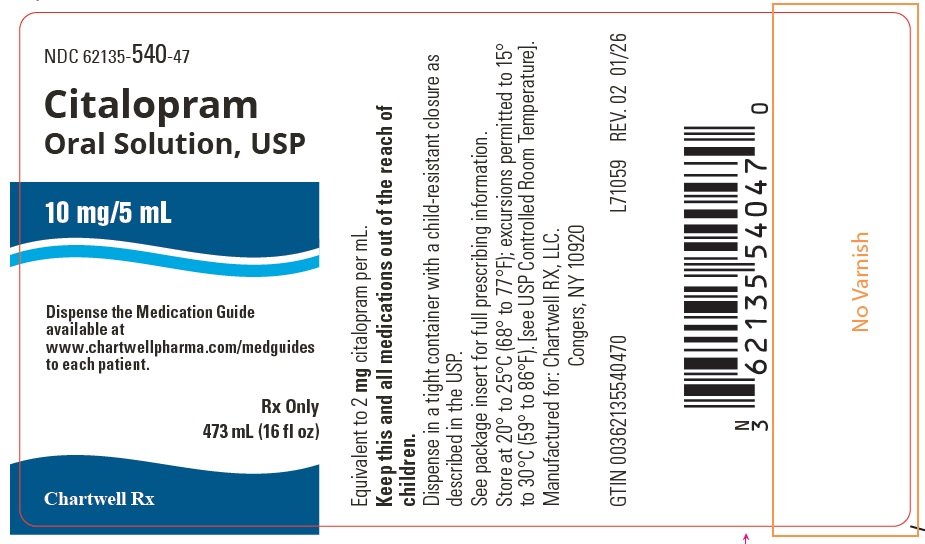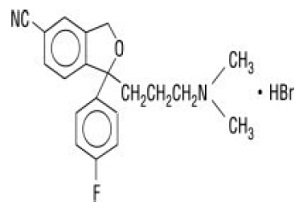 DRUG LABEL: Citalopram
NDC: 62135-540 | Form: SOLUTION
Manufacturer: Chartwell RX, LLC
Category: prescription | Type: HUMAN PRESCRIPTION DRUG LABEL
Date: 20260206

ACTIVE INGREDIENTS: CITALOPRAM HYDROBROMIDE 10 mg/5 mL
INACTIVE INGREDIENTS: SORBITOL; PROPYLENE GLYCOL; METHYLPARABEN; PROPYLPARABEN; WATER

Citalopram Oral Solution, USP
Rx Only

WARNING: SUICIDALITY and ANTIDEPRESSANT DRUGS

Antidepressants increased the risk compared to placebo of suicidal thinking and behavior (suicidality) in children, adolescents, and young adults in short-term studies of major depressive disorder (MDD) and other psychiatric disorders. Anyone considering the use of citalopram or any other antidepressant in a child, adolescent, or young adult must balance this risk with the clinical need. Short-term studies did not show an increase in the risk of suicidality with antidepressants compared to placebo in adults beyond age 24; there was a reduction in risk with antidepressants compared to placebo in adults aged 65 and older. Depression and certain other psychiatric disorders are themselves associated with increases in the risk of suicide. Patients of all ages who are started on antidepressant therapy should be monitored appropriately and observed closely for clinical worsening suicidality, or unusual changes in behavior. Families and caregivers should be advised of the need for close observation and communication with the prescriber. Citalopram is not approved for use in pediatric patients. (See WARNINGS: Clinical Worsening and Suicide Risk, PRECAUTIONS: Information for Patients, and PRECAUTIONS: Pediatric Use.)

DESCRIPTION

Citalopram Oral Solution, USP is an orally administered selective serotonin reuptake inhibitor (SSRI) with a chemical structure unrelated to that of other SSRIs or of tricyclic, tetracyclic, or other available antidepressant agents. Citalopram Hydrobromide, USP is a racemic bicyclic phthalane derivative designated (±)-1-(3-dimethylaminopropyl)-1-(4-fluorophenyl)-1,3-dihydroisobenzofuran-5-carbonitrile, hydrobromide with the following structural formula:

The molecular formula is C20H22BrFN2O and its molecular weight is 405.35.

Citalopram hydrobromide occurs as a fine, white to off-white powder. Citalopram hydrobromide is sparingly soluble in water and soluble in ethanol.

Citalopram hydrobromide is available as a clear, colorless, peppermint flavored oral solution.

Citalopram Oral Solution, USP contains Citalopram hydrobromide equivalent to 2 mg/mL citalopram base. It also contains the following inactive ingredients: sorbitol, purified water, propylene glycol, methylparaben, peppermint flavor, and propylparaben.

CLINICAL PHARMACOLOGY

Pharmacodynamics

The mechanism of action of citalopram as an antidepressant is presumed to be linked to potentiation of serotonergic activity in the central nervous system (CNS) resulting from its inhibition of CNS neuronal reuptake of serotonin (5-HT). In vitroand in vivostudies in animals suggest that citalopram is a highly selective serotonin reuptake inhibitor (SSRI) with minimal effects on norepinephrine (NE) and dopamine (DA) neuronal reuptake. Tolerance to the inhibition of 5-HT uptake is not induced by long-term (14-day) treatment of rats with citalopram. Citalopram is a racemic mixture (50/50), and the inhibition of 5-HT reuptake by citalopram is primarily due to the (S)-enantiomer.

Citalopram has no or very low affinity for 5-HT1A, 5-HT2A, dopamine D1and D2, α1-, α2-, and β-adrenergic, histamine H1, gamma aminobutyric acid (GABA), muscarinic cholinergic, and benzodiazepine receptors. Antagonism of muscarinic, histaminergic, and adrenergic receptors has been hypothesized to be associated with various anticholinergic, sedative, and cardiovascular effects of other psychotropic drugs.

Pharmacokinetics

The single- and multiple-dose pharmacokinetics of citalopram are linear and dose-proportional in a dose range of 10 to 60 mg/day. Biotransformation of citalopram is mainly hepatic, with a mean terminal half-life of about 35 hours. With once daily dosing, steady state plasma concentrations are achieved within approximately one week. At steady state, the extent of accumulation of citalopram in plasma, based on the half-life, is expected to be 2.5 times the plasma concentrations observed after a single dose. The tablet and oral solution dosage forms of citalopram are bioequivalent.

Absorption and Distribution

Following a single 40 mg oral dose of citalopram, peak blood levels occur at about 4 hours. The absolute bioavailability of citalopram was about 80% relative to an intravenous dose, and absorption is not affected by food. The volume of distribution of citalopram is about 12 L/kg and the binding of citalopram (CT), demethylcitalopram (DCT) and didemethylcitalopram (DDCT) to human plasma proteins is about 80%.

Metabolism and Elimination

Following intravenous administrations of citalopram, the fraction of drug recovered in the urine as citalopram and DCT was about 10% and 5%, respectively. The systemic clearance of citalopram was 330 mL/min, with approximately 20% of that due to renal clearance.

Citalopram is metabolized to demethylcitalopram (DCT), didemethylcitalopram (DDCT), citalopram-N-oxide, and a deaminated propionic acid derivative. In humans, unchanged citalopram is the predominant compound in plasma. At steady state, the concentrations of citalopram's metabolites, DCT and DDCT, in plasma are approximately one-half and one-tenth, respectively, that of the parent drug. In vitrostudies show that citalopram is at least 8 times more potent than its metabolites in the inhibition of serotonin reuptake, suggesting that the metabolites evaluated do not likely contribute significantly to the antidepressant actions of citalopram.

In vitrostudies using human liver microsomes indicated that CYP3A4 and CYP2C19 are the primary isozymes involved in the N-demethylation of citalopram.

Population Subgroups

Age: Citalopram pharmacokinetics in subjects ≥ 60 years of age were compared to younger subjects in two normal volunteer studies. In a single-dose study, citalopram AUC and half-life were increased in the subjects ≥ 60 years old by 30% and 50%, respectively, whereas in a multiple-dose study they were increased by 23% and 30%, respectively. 20 mg/day is the maximum recommended dose for patients who are greater than 60 years of age (see WARNINGSand DOSAGE AND ADMINISTRATION), due to the risk of QT prolongation.

Gender: In three pharmacokinetic studies (total N=32), citalopram AUC in women was one and a half to two times that in men. This difference was not observed in five other pharmacokinetic studies (total N=114). In clinical studies, no differences in steady state serum citalopram levels were seen between men (N=237) and women (N=388). There were no gender differences in the pharmacokinetics of DCT and DDCT. No adjustment of dosage on the basis of gender is recommended.

Reduced Hepatic Function: Citalopram oral clearance was reduced by 37% and half-life was doubled in patients with reduced hepatic function compared to normal subjects. 20 mg/day is the maximum recommended dose for hepatically impaired patients (see WARNINGSand DOSAGE AND ADMINISTRATION), due to the risk of QT prolongation.

CYP2C19 Poor Metabolizers: In CYP2C19 poor metabolizers, citalopram steady state Cmaxand AUC was increased by 68% and 107%, respectively. Citalopram 20 mg/day is the maximum recommended dose in CYP2C19 poor metabolizers due to the risk of QT prolongation (see WARNINGSand DOSAGE AND ADMINISTRATION).

CYP2D6 Poor Metabolizers: Citalopram steady state levels were not significantly different in poor metabolizers and extensive metabolizers of CYP2D6.

Reduced Renal Function: In patients with mild to moderate renal function impairment, oral clearance of citalopram was reduced by 17% compared to normal subjects. No adjustment of dosage for such patients is recommended. No information is available about the pharmacokinetics of citalopram in patients with severely reduced renal function (creatinine clearance < 20 mL/min).

Drug-Drug Interactions

In vitroenzyme inhibition data did not reveal an inhibitory effect of citalopram on CYP3A4, -2C9, or -2E1, but did suggest that it is a weak inhibitor of CYP1A2, -2D6, and -2C19. Citalopram would be expected to have little inhibitory effect on in vivometabolism mediated by these enzymes. However, in vivodata to address this question are limited.

CYP3A4 and CYP2C19 Inhibitors: Since CYP3A4 and CYP2C19 are the primary enzymes involved in the metabolism of citalopram, it is expected that potent inhibitors of CYP3A4 (e.g., ketoconazole, itraconazole, and macrolide antibiotics) and potent inhibitors of CYP2C19 (e.g., omeprazole) might decrease the clearance of citalopram. However, co-administration of citalopram and the potent CYP3A4 inhibitor ketoconazole did not significantly affect the pharmacokinetics of citalopram. Citalopram 20 mg/day is the maximum recommended dose in patients taking concomitant cimetidine or another CYP2C19 inhibitor, because of the risk of QT prolongation (see WARNINGSand DOSAGE AND ADMINISTRATION).

CYP2D6 Inhibitors: Co-administration of a drug that inhibits CYP2D6 with citalopram is unlikely to have clinically significant effects on citalopram metabolism, based on the study results in CYP2D6 poor metabolizers.

Clinical Efficacy Trials

The efficacy of citalopram as a treatment for depression was established in two placebo-controlled studies (of 4 to 6 weeks in duration) in adult outpatients (ages 18 to 66) meeting DSM-III or DSM-III-R criteria for major depression. Study 1, a 6-week trial in which patients received fixed citalopram doses of 10, 20, 40, and 60 mg/day, showed that citalopram at doses of 40 and 60 mg/day was effective as measured by the Hamilton Depression Rating Scale (HAMD) total score, the HAMD depressed mood item (Item 1), the Montgomery Asberg Depression Rating Scale, and the Clinical Global Impression (CGI) Severity scale. This study showed no clear effect of the 10 and 20 mg/day doses, and the 60 mg/day dose was not more effective than the 40 mg/day dose. In study 2, a 4-week, placebo-controlled trial in depressed patients, of whom 85% met criteria for melancholia, the initial dose was 20 mg/day, followed by titration to the maximum tolerated dose or a maximum dose of 80 mg/day. Patients treated with citalopram showed significantly greater improvement than placebo patients on the HAMD total score, HAMD item 1, and the CGI Severity score. In three additional placebo-controlled depression trials, the difference in response to treatment between patients receiving citalopram and patients receiving placebo was not statistically significant, possibly due to high spontaneous response rate, smaller sample size, or, in the case of one study, too low a dose.

In two long-term studies, depressed patients who had responded to citalopram during an initial 6 or 8 weeks of acute treatment (fixed doses of 20 or 40 mg/day in one study and flexible doses of 20 to 60 mg/day in the second study) were randomized to continuation of citalopram or to placebo. In both studies, patients receiving continued citalopram treatment experienced significantly lower relapse rates over the subsequent 6 months compared to those receiving placebo. In the fixed-dose study, the decreased rate of depression relapse was similar in patients receiving 20 or 40 mg/day of citalopram.

Analyses of the relationship between treatment outcome and age, gender, and race did not suggest any differential responsiveness on the basis of these patient characteristics.

Comparison of Clinical Trial Results

Highly variable results have been seen in the clinical development of all antidepressant drugs. Furthermore, in those circumstances when the drugs have not been studied in the same controlled clinical trial(s), comparisons among the results of studies evaluating the effectiveness of different antidepressant drug products are inherently unreliable. Because conditions of testing (e.g., patient samples, investigators, doses of the treatments administered and compared, outcome measures, etc.) vary among trials, it is virtually impossible to distinguish a difference in drug effect from a difference due to one of the confounding factors just enumerated.

INDICATIONS AND USAGE

Citalopram Oral Solution is indicated for the treatment of depression.

The efficacy of Citalopram Oral Solution in the treatment of depression was established in 4 to 6 week, controlled trials of outpatients whose diagnosis corresponded most closely to the DSM-III and DSM-III-R category of major depressive disorder (see CLINICAL PHARMACOLOGY).

A major depressive episode (DSM-IV) implies a prominent and relatively persistent (nearly every day for at least 2 weeks) depressed or dysphoric mood that usually interferes with daily functioning, and includes at least five of the following nine symptoms: depressed mood, loss of interest in usual activities, significant change in weight and/or appetite, insomnia or hypersomnia, psychomotor agitation or retardation, increased fatigue, feelings of guilt or worthlessness, slowed thinking or impaired concentration, a suicide attempt or suicidal ideation. The antidepressant action of Citalopram Oral Solution in hospitalized depressed patients has not been adequately studied.

The efficacy of Citalopram Oral Solution in maintaining an antidepressant response for up to 24 weeks following 6 to 8 weeks of acute treatment was demonstrated in two placebo-controlled trials (see CLINICAL PHARMACOLOGY). Nevertheless, the physician who elects to use citalopram oral solution for extended periods should periodically re-evaluate the long-term usefulness of the drug for the individual patient.

CONTRAINDICATIONS

The use of MAOIs intended to treat psychiatric disorders with citalopram or within 14 days of stopping treatment with citalopram is contraindicated because of an increased risk of serotonin syndrome. The use of citalopram within 14 days of stopping an MAOI intended to treat psychiatric disorders is also contraindicated (see WARNINGSand DOSAGE AND ADMINISTRATION).

Starting citalopram in a patient who is being treated with MAOIs such as linezolid or intravenous methylene blue is also contraindicated because of an increased risk of serotonin syndrome (see WARNINGSand DOSAGE AND ADMINISTRATION).

Concomitant use in patients taking pimozide is contraindicated (see PRECAUTIONS).

Citalopram Oral Solution is contraindicated in patients with a hypersensitivity to citalopram or any of the inactive ingredients in Citalopram Oral Solution.

WARNINGS

WARNINGS-Clinical Worsening and Suicide Risk

Clinical Worsening and Suicide Risk

Patients with major depressive disorder (MDD), both adult and pediatric, may experience worsening of their depression and/or the emergence of suicidal ideation and behavior (suicidality) or unusual changes in behavior, whether or not they are taking antidepressant medications, and this risk may persist until significant remission occurs. Suicide is a known risk of depression and certain other psychiatric disorders, and these disorders themselves are the strongest predictors of suicide. There has been a long-standing concern, however, that antidepressants may have a role in inducing worsening of depression and the emergence of suicidality in certain patients during the early phases of treatment.

Pooled analyses of short-term placebo-controlled trials of antidepressant drugs (SSRIs and others) showed that these drugs increase the risk of suicidal thinking and behavior (suicidality) in children, adolescents, and young adults (ages 18 to 24) with major depressive disorder (MDD) and other psychiatric disorders. Short-term studies did not show an increase in the risk of suicidality with antidepressants compared to placebo in adults beyond age 24; there was a reduction with antidepressants compared to placebo in adults aged 65 and older.

The pooled analyses of placebo-controlled trials in children and adolescents with MDD, obsessive compulsive disorder (OCD), or other psychiatric disorders included a total of 24 short-term trials of 9 antidepressant drugs in over 4,400 patients. The pooled analyses of placebo-controlled trials in adults with MDD or other psychiatric disorders included a total of 295 short-term trials (median duration of 2 months) of 11 antidepressant drugs in over 77,000 patients. There was considerable variation in risk of suicidality among drugs, but a tendency toward an increase in the younger patients for almost all drugs studied. There were differences in absolute risk of suicidality across the different indications, with the highest incidence in MDD. The risk differences (drug vs. placebo), however, were relatively stable within age strata and across indications. These risk difference (drug-placebo difference in the number of cases of suicidality per 1,000 patients treated) are provided in TABLE 1.

TABLE 1

Age Range | Drug-Placebo Difference in Number of Cases of Suicidality per 1,000 Patients Treated
 | Increases Compared to Placebo
<18 | 14 additional cases
18 to 24 | 5 additional cases
 | Decreases Compared to Placebo
25 to 64 | 1 fewer case
≥65 | 6 fewer cases

No suicides occurred in any of the pediatric trials. There were suicides in the adult trials, but the number was not sufficient to reach any conclusion about drug effect on suicide.

It is unknown whether the suicidality risk extends to longer-term use, i.e., beyond several months. However, there is substantial evidence from placebo-controlled maintenance trials in adults with depression that the use of antidepressants can delay the recurrence of depression.

All patients being treated with antidepressants for any indication should be monitored appropriately and observed closely for clinical worsening, suicidality, and unusual changes in behavior, especially during the initial few months of a course of drug therapy, or at times of dose changes, either increases or decreases.

The following symptoms, anxiety, agitation, panic attacks, insomnia, irritability, hostility, aggressiveness, impulsivity, akathisia (psychomotor restlessness), hypomania, and mania, have been reported in adult and pediatric patients being treated with antidepressants for major depressive disorder as well as for other indications, both psychiatric and nonpsychiatric. Although a causal link between the emergence of such symptoms and either the worsening of depression and/or the emergence of suicidal impulses has not been established, there is concern that such symptoms may represent precursors to emerging suicidality.

Consideration should be given to changing the therapeutic regimen, including possibly discontinuing the medication, in patients whose depression is persistently worse, or who are experiencing emergent suicidality or symptoms that might be precursors to worsening depression or suicidality, especially if these symptoms are severe, abrupt in onset, or were not part of the patient's presenting symptoms.

If the decision has been made to discontinue treatment, medication should be tapered, as rapidly as is feasible, but with recognition that abrupt discontinuation can be associated with certain symptoms (see PRECAUTIONSand DOSAGE AND ADMINISTRATION: Discontinuation of Treatment with Citalopram Oral Solutionfor a description of the risks of discontinuation of citalopram).

Families and caregivers of patients being treated with antidepressants for major depressive disorder or other indications, both psychiatric and nonpsychiatric, should be alerted about the need to monitor patients for the emergence of agitation, irritability, unusual changes in behavior, and the other symptoms described above, as well as the emergence of suicidality, and to report such symptoms immediately to healthcare providers. Such monitoring should include daily observation by families and caregivers.

Prescriptions for citalopram should be written for the smallest quantity consistent with good patient management, in order to reduce the risk of overdose.

QT-Prolongation and Torsade de Pointes

Citalopram causes dose-dependent QTc prolongation, an ECG abnormality that has been associated with Torsade de Pointes(TdP), ventricular tachycardia, and sudden death, all of which have been observed in postmarketing reports for citalopram.

Individually corrected QTc (QTcNi) interval was evaluated in a randomized, placebo and active (moxifloxacin 400 mg) controlled cross-over, escalating multiple-dose study in 119 healthy subjects. The maximum mean (upper bound of the 95% one-sided confidence interval) difference from placebo were 8.5 (10.8) and 18.5 (21) msec or 20 mg and 60 mg citalopram, respectively. Based on the established exposure-response relationship, the predicted QTcNi change from placebo (upper bound of the 95% one-sided confidence interval) under the Cmaxfor the dose of 40 mg is 12.6 (14.3) msec.

Because of the risk of QTc prolongation at higher citalopram doses, it is recommended that citalopram should not be given at doses above 40 mg/day.

It is recommended that citalopram should not be used in patients with congenital long QT syndrome, bradycardia, hypokalemia or hypomagnesemia, recent acute myocardial infarction, or uncompensated heart failure. Citalopram should also not be used in patients who are taking other drugs that prolong the QTc interval. Such drugs include Class 1A (e.g., quinidine, procainamide) or Class III (e.g., amiodarone, sotalol) antiarrhythmic medications, antipsychotic medications (e.g., chlorpromazine, thioridazine), antibiotics (e.g., gatifloxacin, moxifloxacin), or any other class of medications known to prolong the QTc interval (e.g., pentamidine, levomethadyl acetate, methadone).

The citalopram dose should be limited in certain populations. The maximum dose should be limited to 20 mg/day in patients who are CYP2C19 poor metabolizers or those patients who may be taking concomitant cimetidine or another CYP2C19 inhibitor, since higher citalopram exposures would be expected. The maximum dose should also be limited to 20 mg/day in patients with hepatic impairment and in patients who are greater than 60 years of age because of expected higher exposures.

Electrolyte and/or ECG monitoring is recommended in certain circumstances. Patients being considered for citalopram treatment who are at risk for significant electrolyte disturbances should have baseline serum potassium and magnesium measurements with periodic monitoring. Hypokalemia (and/or hypomagnesemia) may increase the risk of QTc prolongation and arrhythmia and should be corrected prior to initiation of treatment and periodically monitored. ECG monitoring is recommended in patients for whom citalopram use is not recommended (see above), but, nevertheless, considered essential. These include those patients with the cardiac conditions noted above, and those taking other drugs that may prolong the QTc interval.

Citalopram should be discontinued in patients who are found to have persistent QTc measurements >500 ms. If patients taking citalopram experience symptoms that could indicate the occurrence of cardiac arrhythmias, e.g., dizziness, palpitations, or syncope, the prescriber should initiate further evaluation, including cardiac monitoring.

Screening Patients for Bipolar Disorder

A major depressive episode may be the initial presentation of bipolar disorder. It is generally believed (though not established in controlled trials) that treating such an episode with an antidepressant alone may increase the likelihood of precipitation of a mixed/manic episode in patients at risk for bipolar disorder. Whether any of the symptoms described above represent such a conversion is unknown. However, prior to initiating treatment with an antidepressant, patients with depressive symptoms should be adequately screened to determine if they are at risk for bipolar disorder; such screening should include a detailed psychiatric history, including a family history of suicide, bipolar disorder, and depression. It should be noted that citalopram is not approved for use in treating bipolar depression.

Serotonin Syndrome

Serotonin-norepinephrine reuptake inhibitors (SNRIs) and selective serotonin reuptake inhibitors (SSRIs), including Citalopram Oral Solution can precipitate serotonin syndrome, a potentially life-threatening condition. The risk is increased with concomitant use of other serotonergic drugs (including triptans, tricyclic antidepressants, fentanyl, lithium, tramadol, tryptophan, meperidine, methadone, buspirone, amphetamines, and St. John’s Wort) and with drugs that impair metabolism of serotonin, i.e., MAOIs [See Contraindications, Drug Interactions]. Serotonin syndrome can also occur when these drugs are used alone.

Serotonin syndrome signs and symptoms may include mental status changes (e.g., agitation, hallucinations, delirium, and coma), autonomic instability (e.g., tachycardia, labile blood pressure, dizziness, diaphoresis, flushing, hyperthermia), neuromuscular symptoms (e.g., tremor, rigidity, myoclonus, hyperreflexia, incoordination), seizures, and gastrointestinal symptoms (e.g., nausea, vomiting, diarrhea).

The concomitant use of Citalopram Oral Solution with MAOIs is contraindicated. In addition, do not initiate Citalopram Oral Solution in a patient being treated with MAOIs such as linezolid or intravenous methylene blue. No reports involved the administration of methylene blue by other routes (such as oral tablets or local tissue injection). If it is necessary to initiate treatment with an MAOI such as linezolid or intravenous methylene blue in a patient taking Citalopram Oral Solution discontinue Citalopram Oral Solution before initiating treatment with the MAOI [See Contraindications, Drug Interactions].

Angle-Closure Glaucoma

The pupillary dilation that occurs following use of many antidepressant drugs including citalopram may trigger an angle closure attack in a patient with anatomically narrow angles who does not have a patent iridectomy.

Sexual Dysfunction

Use of SSRIs, including citalopram, may cause symptoms of sexual dysfunction (see ADVERSE REACTIONS). In male patients, SSRI use may result in ejaculatory delay or failure, decreased libido, and erectile dysfunction. In female patients, SSRI use may result in decreased libido and delayed or absent orgasm.

It is important for prescribers to inquire about sexual function prior to initiation of citalopram and to inquire specifically about changes in sexual function during treatment, because sexual function may not be spontaneously reported. When evaluating changes in sexual function, obtaining a detailed history (including timing of symptom onset) is important because sexual symptoms may have other causes, including the underlying psychiatric disorder. Discuss potential management strategies to support patients in making informed decisions about treatment.

PRECAUTIONS

General

Discontinuation of Treatment with Citalopram

During marketing of citalopram and other SSRIs and SNRIs (serotonin and norepinephrine reuptake inhibitors), there have been spontaneous reports of adverse events occurring upon discontinuation of these drugs, particularly when abrupt, including the following: dysphoric mood, irritability, agitation, dizziness, sensory disturbances (e.g., paresthesias such as electric shock sensations), anxiety, confusion, headache, lethargy, emotional lability, insomnia, and hypomania. While these events are generally self-limiting, there have been reports of serious discontinuation symptoms.

Patients should be monitored for these symptoms when discontinuing treatment with citalopram. A gradual reduction in the dose rather than abrupt cessation is recommended whenever possible. If intolerable symptoms occur following a decrease in the dose or upon discontinuation of treatment, then resuming the previously prescribed dose may be considered. Subsequently, the physician may continue decreasing the dose but at a more gradual rate (see DOSAGE AND ADMINISTRATION).

Abnormal Bleeding

SSRIs and SNRIs, including citalopram, may increase the risk of bleeding events. Concomitant use of aspirin, nonsteroidal anti-inflammatory drugs, warfarin, and other anticoagulants may add to the risk. Case reports and epidemiological studies (case-control and cohort design) have demonstrated an association between use of drugs that interfere with serotonin reuptake and the occurrence of gastrointestinal bleeding. Based on data from the published observational studies, exposure to SSRIs, particularly in the month before delivery, has been associated with a less than 2-fold increase in the risk of postpartum hemorrhage (see PRECAUTIONS: Pregnancy).Bleeding events related to SSRIs and SNRIs use have ranged from ecchymoses, hematomas, epistaxis, and petechiae to life-threatening hemorrhages.

Patients should be cautioned about the increased risk of bleeding associated with the concomitant use of citalopram with NSAIDs, aspirin, or other drugs that affect coagulation.

Hyponatremia

Hyponatremia may occur as a result of treatment with SSRIs and SNRIs, including citalopram. In many cases, this hyponatremia appears to be the result of the syndrome of inappropriate antidiuretic hormone secretion (SIADH) and was reversible when citalopram was discontinued. Cases with serum sodium lower than 110 mmol/L have been reported. Elderly patients may be at greater risk of developing hyponatremia with SSRIs and SNRIs. Also, patients taking diuretics or who are otherwise volume depleted may be at greater risk (see Geriatric Use). Discontinuation of citalopram should be considered in patients with symptomatic hyponatremia and appropriate medical intervention should be instituted.

Signs and symptoms of hyponatremia include headache, difficulty concentrating, memory impairment, confusion, weakness, and unsteadiness, which may lead to falls. Signs and symptoms associated with more severe and/or acute cases have included hallucination, syncope, seizure, coma, respiratory arrest, and death.

Activation of Mania/Hypomania

In placebo-controlled trials of citalopram, some of which included patients with bipolar disorder, activation of mania/hypomania was reported in 0.2% of 1,063 patients treated with citalopram and in none of the 446 patients treated with placebo. Activation of mania/hypomania has also been reported in a small proportion of patients with major affective disorders treated with other marketed antidepressants. As with all antidepressants, citalopram should be used cautiously in patients with a history of mania.

Seizures

Although anticonvulsant effects of citalopram have been observed in animal studies, citalopram has not been systematically evaluated in patients with a seizure disorder. These patients were excluded from clinical studies during the product's premarketing testing. In clinical trials of citalopram, seizures occurred in 0.3% of patients treated with citalopram (a rate of one patient per 98 years of exposure) and 0.5% of patients treated with placebo (a rate of one patient per 50 years of exposure). Like other antidepressants, citalopram should be introduced with care in patients with a history of seizure disorder.

Interference with Cognitive and Motor Performance

In studies in normal volunteers, citalopram in doses of 40 mg/day did not produce impairment of intellectual function or psychomotor performance. Because any psychoactive drug may impair judgment, thinking, or motor skills, however, patients should be cautioned about operating hazardous machinery, including automobiles, until they are reasonably certain that citalopram therapy does not affect their ability to engage in such activities.

Use in Patients with Concomitant Illness

Clinical experience with citalopram in patients with certain concomitant systemic illnesses is limited. Due to the risk of QT prolongation, citalopram use should be avoided in patients with certain cardiac conditions, and ECG monitoring is advised if citalopram must be used in such patients. Electrolytes should be monitored in treating patients with diseases or conditions that cause hypokalemia or hypomagnesemia (see WARNINGS).

In subjects with hepatic impairment, citalopram clearance was decreased and plasma concentrations were increased. The use of citalopram in hepatically impaired patients should be approached with caution and a lower maximum dosage is recommended (see DOSAGE AND ADMINISTRATION).

Because citalopram is extensively metabolized, excretion of unchanged drug in urine is a minor route of elimination. Until adequate numbers of patients with severe renal impairment have been evaluated during chronic treatment with citalopram, however, it should be used with caution in such patients (see DOSAGE AND ADMINISTRATION).

Information for Patients

Physicians are advised to discuss the following issues with patients for whom they prescribe citalopram:

Although in controlled studies citalopram has not been shown to impair psychomotor performance, any psychoactive drug may impair judgment, thinking, or motor skills, so patients should be cautioned about operating hazardous machinery, including automobiles, until they are reasonably certain that citalopram therapy does not affect their ability to engage in such activities.

Patients should be told that, although citalopram has not been shown in experiments with normal subjects to increase the mental and motor skill impairments caused by alcohol, the concomitant use of citalopram and alcohol in depressed patients is not advised.

Patients should be advised to inform their physician if they are taking, or plan to take, any prescription or over-the-counter drugs, as there is a potential for interactions.

Patients should be cautioned about the concomitant use of citalopram and NSAIDs, aspirin, warfarin, or other drugs that affect coagulation since the combined use of psychotropic drugs that interfere with serotonin reuptake and these agents has been associated with an increased risk of bleeding.

Patients should be advised to notify their physician if they become pregnant or intend to become pregnant during therapy.

Patients should be advised to notify their physician if they are breastfeeding an infant.

While patients may notice improvement with citalopram therapy in 1 to 4 weeks, they should be advised to continue therapy as directed.

Prescribers or other health professionals should inform patients, their families, and their caregivers about the benefits and risks associated with treatment with citalopram and should counsel them in its appropriate use. A patient Medication Guide about “Antidepressant Medicines, Depression and other Serious Mental Illness, and Suicidal Thoughts or Actions” is available for citalopram. The prescriber or health professional should instruct patients, their families, and their caregivers to read the Medication Guide and should assist them in understanding its contents. Patients should be given the opportunity to discuss the contents of the Medication Guide and to obtain answers to any questions they may have.

Patients should be advised of the following issues and asked to alert their prescriber if these occur while taking citalopram.

Patients should be advised that taking citalopram can cause mild pupillary dilation, which in susceptible individuals, can lead to an episode of angle-closure glaucoma. Pre-existing glaucoma is almost always open-angle glaucoma because angle-closure glaucoma, when diagnosed, can be treated definitively with iridectomy. Open-angle glaucoma is not a risk factor for angle closure glaucoma. Patients may wish to be examined to determine whether they are susceptible to angle closure, and have a prophylactic procedure (e.g., iridectomy), if they are susceptible.

Serotonin Syndrome

Caution patients about the risk of serotonin syndrome, particularly with the concomitant use of Citalopram Oral Solution with other serotonergic drugs including triptans, tricyclic antidepressants, opioids, lithium, tryptophan, buspirone, amphetamines, St. John’s Wort, and with drugs that impair metabolism of serotonin (in particular, MAOIs, both those intended to treat psychiatric disorders and also others, such as linezolid). Instruct patients to contact their health care provider or report to the emergency room if they experience signs or symptoms of serotonin syndrome [see Warnings, Drug Interactions].

Clinical Worsening and Suicide Risk

Patients, their families, and their caregivers should be encouraged to be alert to the emergence of anxiety, agitation, panic attacks, insomnia, irritability, hostility, aggressiveness, impulsivity, akathisia (psychomotor restlessness), hypomania, mania, other unusual changes in behavior, worsening of depression, and suicidal ideation, especially early during antidepressant treatment and when the dose is adjusted up or down. Families and caregivers of patients should be advised to look for the emergence of such symptoms on a day-to-day basis, since changes may be abrupt. Such symptoms should be reported to the patient’s prescriber or health professional, especially if they are severe, abrupt in onset, or were not part of the patient’s presenting symptoms. Symptoms such as these may be associated with an increased risk for suicidal thinking and behavior and indicate a need for very close monitoring and possibly changes in the medication.

Sexual Dysfunction

Advise patients that use of citalopram may cause symptoms of sexual dysfunction in both male and female patients. Inform patients that they should discuss any changes in sexual function and potential management strategies with their healthcare provider (see WARNINGS).

Laboratory Tests

There are no specific laboratory tests recommended.

Drug Interactions

Serotonergic Drugs

Based on the mechanism of action of SNRIs and SSRIs, including citalopram hydrobromide, and the potential for serotonin syndrome, caution is advised when citalopram is co-administered with other drugs that may affect the serotonergic neurotransmitter systems, such as triptans, lithium, opioids, amphetamines, or St. John’s Wort (see WARNINGS; Serotonin Syndrome).

Triptans

There have been rare postmarketing reports of serotonin syndrome with use of an SSRI and a triptan. If concomitant treatment of citalopram with a triptan is clinically warranted, careful observation of the patient is advised, particularly during treatment initiation and dose increases (see WARNINGS; Serotonin Syndrome).

CNS Drugs

Given the primary CNS effects of citalopram, caution should be used when it is taken in combination with other centrally acting drugs.

Alcohol

Although citalopram did not potentiate the cognitive and motor effects of alcohol in a clinical trial, as with other psychotropic medications, the use of alcohol by depressed patients taking citalopram is not recommended.

Monoamine Oxidase Inhibitors (MAOIs)

See CONTRAINDICATIONSand WARNINGSand DOSAGE AND ADMINISTRATION.

Drugs That Interfere with Hemostasis (NSAIDs, Aspirin, Warfarin, etc.)

Serotonin release by platelets plays an important role in hemostasis. Epidemiological studies of the case-control and cohort design that have demonstrated an association between use of psychotropic drugs that interfere with serotonin reuptake and the occurrence of upper gastrointestinal bleeding have also shown that concurrent use of an NSAID or aspirin may potentiate the risk of bleeding. Altered anticoagulant effects, including increased bleeding, have been reported when SSRIs and SNRIs are co-administered with warfarin. Patients receiving warfarin therapy should be carefully monitored when citalopram is initiated or discontinued.

Cimetidine

In subjects who had received 21 days of 40 mg/day citalopram, combined administration of 400 mg/day cimetidine for 8 days resulted in an increase in citalopram AUC and Cmaxof 43% and 39%, respectively.

Citalopram 20 mg/day is the maximum recommended dose for patients taking concomitant cimetidine because of the risk of QT prolongation (see WARNINGSand DOSAGE AND ADMINISTRATION).

Digoxin

In subjects who had received 21 days of 40 mg/day citalopram, combined administration of citalopram and digoxin (single dose of 1 mg) did not significantly affect the pharmacokinetics of either citalopram or digoxin.

Lithium

Co-administration of citalopram (40 mg/day for 10 days) and lithium (30 mmol/day for 5 days) had no significant effect on the pharmacokinetics of citalopram or lithium. Nevertheless, plasma lithium levels should be monitored with appropriate adjustment to the lithium dose in accordance with standard clinical practice. Because lithium may enhance the serotonergic effects of citalopram, caution should be exercised when citalopram and lithium are co-administered.

Pimozide

In a controlled study, a single dose of pimozide 2 mg co-administered with citalopram 40 mg given once daily for 11 days was associated with a mean increase in QTc values of approximately 10 msec compared to pimozide given alone. Citalopram did not alter the mean AUC or Cmaxof pimozide. The mechanism of this pharmacodynamic interaction is not known.

Theophylline

Combined administration of citalopram (40 mg/day for 21 days) and the CYP1A2 substrate theophylline (single dose of 300 mg) did not affect the pharmacokinetics of theophylline. The effect of theophylline on the pharmacokinetics of citalopram was not evaluated.

Sumatriptan

There have been rare postmarketing reports describing patients with weakness, hyperreflexia, and incoordination following the use of a SSRI and sumatriptan. If concomitant treatment with sumatriptan and a SSRI (e.g., fluoxetine, fluvoxamine, paroxetine, sertraline, citalopram) is clinically warranted, appropriate observation of the patient is advised.

Warfarin

Administration of 40 mg/day citalopram for 21 days did not affect the pharmacokinetics of warfarin, a CYP3A4 substrate. Prothrombin time was increased by 5%, the clinical significance of which is unknown.

Carbamazepine

Combined administration of citalopram (40 mg/day for 14 days) and carbamazepine (titrated to 400 mg/day for 35 days) did not significantly affect the pharmacokinetics of carbamazepine, a CYP3A4 substrate. Although trough citalopram plasma levels were unaffected, given the enzyme-inducing properties of carbamazepine, the possibility that carbamazepine might increase the clearance of citalopram should be considered if the two drugs are co-administered.

Triazolam

Combined administration of citalopram (titrated to 40 mg/day for 28 days) and the CYP3A4 substrate triazolam (single dose of 0.25 mg) did not significantly affect the pharmacokinetics of either citalopram or triazolam.

Ketoconazole

Combined administration of citalopram (40 mg) and ketoconazole (200 mg) decreased the Cmaxand AUC of ketoconazole by 21% and 10%, respectively, and did not significantly affect the pharmacokinetics of citalopram.

CYP2C19 Inhibitors

Citalopram 20 mg/day is the maximum recommended dose for patients taking concomitant CYP2C19 inhibitors because of the risk of QT prolongation (see WARNINGS, DOSAGE AND ADMINISTRATION, and CLINICAL PHARMACOLOGY).

Metoprolol

Administration of 40 mg/day citalopram for 22 days resulted in a two-fold increase in the plasma levels of the beta-adrenergic blocker metoprolol. Increased metoprolol plasma levels have been associated with decreased cardioselectivity. Co-administration of citalopram and metoprolol had no clinically significant effects on blood pressure or heart rate.

Imipramine and Other Tricyclic Antidepressants (TCAs)

In vitrostudies suggest that citalopram is a relatively weak inhibitor of CYP2D6. Co-administration of citalopram (40 mg/day for 10 days) with the TCA imipramine (single dose of 100 mg), a substrate for CYP2D6, did not significantly affect the plasma concentrations of imipramine or citalopram. However, the concentration of the imipramine metabolite desipramine was increased by approximately 50%. The clinical significance of the desipramine change is unknown. Nevertheless, caution is indicated in the co-administration of TCA's with citalopram.

Electroconvulsive Therapy (ECT)

There are no clinical studies of the combined use of electroconvulsive therapy (ECT) and citalopram.

Carcinogenesis, Mutagenesis, Impairment of Fertility

Carcinogenesis

Citalopram was administered in the diet to NMRI/BOM strain mice and COBS WI strain rats for 18 and 24 months, respectively. There was no evidence for carcinogenicity of citalopram in mice receiving up to 240 mg/kg/day, which is equivalent to 20 times the maximum recommended human daily dose (MRHD) of 60 mg on a surface area (mg/m^2) basis. There was an increased incidence of small intestine carcinoma in rats receiving 8 or 24 mg/kg/day, doses which are approximately 1.3 and 4 times the MRHD, respectively, on a mg/m^2basis. A no-effect dose for this finding was not established. The relevance of these findings to humans is unknown.

Mutagenesis

Citalopram was mutagenic in the in vitrobacterial reverse mutation assay (Ames test) in 2 of 5 bacterial strains (Salmonella TA98 and TA1537) in the absence of metabolic activation. It was clastogenic in the in vitroChinese hamster lung cell assay for chromosomal aberrations in the presence and absence of metabolic activation. Citalopram was not mutagenic in the in vitromammalian forward gene mutation assay (HPRT) in mouse lymphoma cells or in a coupled in vitro/in vivounscheduled DNA synthesis (UDS) assay in rat liver. It was not clastogenic in the in vitrochromosomal aberration assay in human lymphocytes or in two in vivomouse micronucleus assays.

Impairment of Fertility

When citalopram was administered orally to 16 male and 24 female rats prior to and throughout mating and gestation at doses of 32, 48, and 72 mg/kg/day, mating was decreased at all doses, and fertility was decreased at doses ≥ 32 mg/kg/day, approximately 5 times the MRHD of 60 mg/day on a body surface area (mg/m^2) basis. Gestation duration was increased at 48 mg/kg/day, approximately 8 times the MRHD.

Pregnancy

In animal reproduction studies, citalopram has been shown to have adverse effects on embryo/fetal and postnatal development, including teratogenic effects, when administered at doses greater than human therapeutic doses.

In two rat embryo/fetal development studies, oral administration of citalopram (32, 56, or 112 mg/kg/day) to pregnant animals during the period of organogenesis resulted in decreased embryo/fetal growth and survival and an increased incidence of fetal abnormalities (including cardiovascular and skeletal defects) at the high dose, which is approximately 18 times the MRHD of 60 mg/day on a body surface area (mg/m^2) basis. This dose was also associated with maternal toxicity (clinical signs, decreased body weight gain). The developmental no-effect dose of 56 mg/kg/day is approximately 9 times the MRHD on a mg/m^2basis. In a rabbit study, no adverse effects on embryo/fetal development were observed at doses of up to 16 mg/kg/day, or approximately 5 times the MRHD on a mg/m^2basis. Thus, teratogenic effects were observed at a maternally toxic dose in the rat and were not observed in the rabbit.

When female rats were treated with citalopram (4.8, 12.8, or 32 mg/kg/day) from late gestation through weaning, increased offspring mortality during the first 4 days after birth and persistent offspring growth retardation were observed at the highest dose, which is approximately 5 times the MRHD on a mg/m^2basis. The no-effect dose of 12.8 mg/kg/day is approximately 2 times the MRHD on a mg/m^2basis. Similar effects on offspring mortality and growth were seen when dams were treated throughout gestation and early lactation at doses ≥ 24 mg/kg/day, approximately 4 times the MRHD on a mg/m^2basis. A no-effect dose was not determined in that study.

There are no adequate and well-controlled studies in pregnant women; therefore, citalopram should be used during pregnancy only if the potential benefit justifies the potential risk to the fetus.

Pregnancy-Nonteratogenic Effects

Based on data from published observational studies, exposure to SSRIs, particularly in the month before delivery, has been associated with a less than 2-fold increase in the risk of postpartum hemorrhage (see PRECAUTIONS: Abnormal Bleeding).

Neonates exposed to citalopram and other SSRIs or serotonin and norepinephrine reuptake inhibitors (SNRIs), late in the third trimester, have developed complications requiring prolonged hospitalization, respiratory support, and tube feeding. Such complications can arise immediately upon delivery. Reported clinical findings have included respiratory distress, cyanosis, apnea, seizures, temperature instability, feeding difficulty, vomiting, hypoglycemia, hypotonia, hypertonia, hyperreflexia, tremor, jitteriness, irritability, and constant crying. These features are consistent with either a direct toxic effect of SSRIs and SNRIs or, possibly, a drug discontinuation syndrome. It should be noted that, in some cases, the clinical picture is consistent with serotonin syndrome (see WARNINGS; Serotonin Syndrome).

Infants exposed to SSRIs in pregnancy may have an increased risk for persistent pulmonary hypertension of the newborn (PPHN). PPHN occurs in 1-2 per 1,000 live births in the general population and is associated with substantial neonatal morbidity and mortality. Several recent epidemiologic studies suggest a positive statistical association between SSRI use (including citalopram) in pregnancy and PPHN. Other studies do not show a significant statistical association.

Physicians should also note the results of a prospective longitudinal study of 201 pregnant women with a history of major depression, who were either on antidepressants or had received antidepressants less than 12 weeks prior to their last menstrual period, and were in remission. Women who discontinued antidepressant medication during pregnancy showed a significant increase in relapse of their major depression compared to those women who remained on antidepressant medication throughout pregnancy.

When treating a pregnant woman with citalopram, the physician should carefully consider both the potential risks of taking an SSRI, along with the established benefits of treating depression with an antidepressant. This decision can only be made on a case by case basis (see DOSAGE AND ADMINISTRATION).

Maternal Adverse Reactions

Use of Citalopram Oral Solution in the month before delivery may be associated with an increased risk of postpartum hemorrhage (see PRECAUTIONS, Abnormal Bleeding).

Labor and Delivery

The effect of citalopram on labor and delivery in humans is unknown.

Nursing Mothers

As has been found to occur with many other drugs, citalopram is excreted in human breast milk. There have been two reports of infants experiencing excessive somnolence, decreased feeding, and weight loss in association with breastfeeding from a citalopram-treated mother; in one case, the infant was reported to recover completely upon discontinuation of citalopram by its mother, and in the second case, no follow-up information was available. The decision whether to continue or discontinue either nursing or citalopram therapy should take into account the risks of citalopram exposure for the infant and the benefits of citalopram treatment for the mother.

Pediatric Use

Safety and effectiveness in the pediatric population have not been established (see BOXED WARNINGand WARNINGS: Clinical Worsening and Suicide Risk). Two placebo-controlled trials in 407 pediatric patients with MDD have been conducted with citalopram, and the data were not sufficient to support a claim for use in pediatric patients. Anyone considering the use of citalopram in a child or adolescent must balance the potential risks with the clinical need.

Decreased appetite and weight loss have been observed in association with the use of SSRIs. Consequently, regular monitoring of weight and growth should be performed in children and adolescents treated with citalopram.

Geriatric Use

Of 4,422 patients in clinical studies of citalopram, 1,357 were 60 and over, 1,034 were 65 and over, and 457 were 75 and over. No overall differences in safety or effectiveness were observed between these subjects and younger subjects, and other reported clinical experience has not identified differences in responses between the elderly and younger patients, but greater sensitivity of some older individuals cannot be ruled out. Most elderly patients treated with citalopram in clinical trials received daily doses between 20 and 40 mg (see DOSAGE AND ADMINISTRATION).

SSRIs and SNRIs, including citalopram, have been associated with cases of clinically significant hyponatremia in elderly patients, who may be at greater risk for this adverse event (see PRECAUTIONS: General).

In two pharmacokinetic studies, citalopram AUC was increased by 23% and 30%, respectively, in subjects ≥ 60 years of age as compared to younger subjects, and its half-life was increased by 30% and 50%, respectively (see CLINICAL PHARMACOLOGY).

20 mg/day is the maximum recommended dose for patients who are greater than 60 years of age (see WARNINGSand DOSAGE AND ADMINISTRATION).

ADVERSE REACTIONS

The premarketing development program for citalopram included citalopram exposures in patients and/or normal subjects from 3 different groups of studies: 429 normal subjects in clinical pharmacology/pharmacokinetic studies; 4,422 exposures from patients in controlled and uncontrolled clinical trials, corresponding to approximately 1,370 patient-exposure years. There were, in addition, over 19,000 exposures from mostly open-label, European postmarketing studies. The conditions and duration of treatment with citalopram varied greatly and included (in overlapping categories) open-label and double-blind studies, inpatient and outpatient studies, fixed-dose and dose-titration studies, and short-term and long-term exposure. Adverse reactions were assessed by collecting adverse events, results of physical examinations, vital signs, weights, laboratory analyses, ECGs, and results of ophthalmologic examinations.

Adverse events during exposure were obtained primarily by general inquiry and recorded by clinical investigators using terminology of their own choosing. Consequently, it is not possible to provide a meaningful estimate of the proportion of individuals experiencing adverse events without first grouping similar types of events into a smaller number of standardized event categories. In the tables and tabulations that follow, standard World Health Organization (WHO) terminology has been used to classify reported adverse events.

The stated frequencies of adverse events represent the proportion of individuals who experienced, at least once, a treatment-emergent adverse event of the type listed. An event was considered treatment-emergent if it occurred for the first time or worsened while receiving therapy following baseline evaluation.

Adverse Findings Observed in Short-Term, Placebo-Controlled Trials

Adverse Events Associated with Discontinuation of Treatment

Among 1,063 depressed patients who received citalopram at doses ranging from 10 to 80 mg/day in placebo-controlled trials of up to 6 weeks in duration, 16% discontinued treatment due to an adverse event, as compared to 8% of 446 patients receiving placebo. The adverse events associated with discontinuation and considered drug-related (i.e., associated with discontinuation in at least 1% of citalopram-treated patients at a rate at least twice that of placebo) are shown in TABLE 2. It should be noted that one patient can report more than one reason for discontinuation and be counted more than once in this table.

TABLE 2: Adverse Events Associated with Discontinuation of Treatment in Short-Term, Placebo-Controlled, Depression Trials

 |  | Percentage of Patients Discontinuing Due to Adverse Event
Body System/Adverse Event | Citalopram (N=1,063) |  | Placebo (N=446)
General
Asthenia | 1% |  | <1%
Gastrointestinal Disorders
Nausea | 4% |  | 0%
Dry Mouth | 1% |  | <1%
Vomiting | 1% |  | 0%
Central and Peripheral Nervous System Disorders
Dizziness | 2% |  | <1%
Psychiatric Disorders
Insomnia | 3% |  | 1%
Somnolence | 2% |  | 1%
Agitation | 1% |  | <1%

Adverse Events Occurring at an Incidence of 2% or More Among Citalopram-Treated Patients

TABLE 3 enumerates the incidence, rounded to the nearest percent, of treatment-emergent adverse events that occurred among 1,063 depressed patients who received citalopram at doses ranging from 10 to 80 mg/day in placebo-controlled trials of up to 6 weeks in duration. Events included are those occurring in 2% or more of patients treated with citalopram and for which the incidence in patients treated with citalopram was greater than the incidence in placebo-treated patients.

The prescriber should be aware that these figures cannot be used to predict the incidence of adverse events in the course of usual medical practice where patient characteristics and other factors differ from those which prevailed in the clinical trials. Similarly, the cited frequencies cannot be compared with figures obtained from other clinical investigations involving different treatments, uses, and investigators. The cited figures, however, do provide the prescribing physician with some basis for estimating the relative contribution of drug and non-drug factors to the adverse event incidence rate in the population studied.

The only commonly observed adverse event that occurred in citalopram patients with an incidence of 5% or greater and at least twice the incidence in placebo patients was ejaculation disorder (primarily ejaculatory delay) in male patients (see TABLE 3).

TABLE 3: Treatment-Emergent Adverse Events: Incidence in Placebo-Controlled Clinical Trials*

 |  | (Percentage of Patients Reporting Event)
Body System/Adverse Event | Citalopram (N=1,063) |  | Placebo (N=446)
Autonomic Nervous System Disorders
Dry Mouth | 20% |  | 14%
Sweating Increased | 11% |  | 9%
Central & Peripheral Nervous System Disorders
Tremor | 8% |  | 6%
Gastrointestinal Disorders
Nausea | 21% |  | 14%
Diarrhea | 8% |  | 5%
Dyspepsia | 5% |  | 4%
Vomiting | 4% |  | 3%
Abdominal Pain | 3% |  | 2%
General
Fatigue | 5% |  | 3%
Fever | 2% |  | < 1%
Musculoskeletal System Disorders
Arthralgia | 2% |  | 1%
Myalgia | 2% |  | 1%
Psychiatric Disorders
Somnolence | 18% |  | 10%
Insomnia | 15% |  | 14%
Anxiety | 4% |  | 3%
Anorexia | 4% |  | 2%
Agitation | 3% |  | 1%
Dysmenorrhea^1 | 3% |  | 2%
Libido Decreased | 2% |  | < 1%
Yawning | 2% |  | < 1%
Respiratory System Disorders
Upper Respiratory Tract Infection | 5% |  | 4%
Rhinitis | 5% |  | 3%
Sinusitis | 3% |  | < 1%
Urogenital
Ejaculation Disorder^2,3 | 6% |  | 1%
Impotence^3 | 3% |  | <1%

*Events reported by at least 2% of patients treated with citalopram are reported, except for the following events which had an incidence on placebo ≥ citalopram: headache, asthenia, dizziness, constipation, palpitation, vision abnormal, sleep disorder, nervousness, pharyngitis, micturition disorder, back pain.

^1Denominator used was for females only (N=638 citalopram; N=252 placebo).

^2Primarily ejaculatory delay.

^3Denominator used was for males only (N=425 citalopram; N=194 placebo).

Dose Dependency of Adverse Events

The potential relationship between the dose of citalopram administered and the incidence of adverse events was examined in a fixed-dose study in depressed patients receiving placebo or citalopram 10, 20, 40, and 60 mg. Jonckheere's trend test revealed a positive dose response (p<0.05) for the following adverse events: fatigue, impotence, insomnia, sweating increased, somnolence, and yawning.

Male and Female Sexual Dysfunction with SSRIs

Although changes in sexual desire, sexual performance, and sexual satisfaction often occur as manifestations of a psychiatric disorder, they may also be a consequence of pharmacologic treatment. In particular, some evidence suggests that SSRIs can cause such untoward sexual experiences.

Reliable estimates of the incidence and severity of untoward experiences involving sexual desire, performance, and satisfaction are difficult to obtain, however, in part because patients and physicians may be reluctant to discuss them. Accordingly, estimates of the incidence of untoward sexual experience and performance cited in product labeling, are likely to underestimate their actual incidence.

The table below displays the incidence of sexual side effects reported by at least 2% of patients taking citalopram in a pool of placebo-controlled clinical trials in patients with depression.

Treatment | Citalopram (425 males) | Placebo (194 males)
Abnormal Ejaculation (mostly ejaculatory delay) | 6.1% (males only) | 1% (males only)
Decreased Libido | 3.8% (males only) | <1% (males only)
Impotence | 2.8% (males only) | <1% (males only)

In female depressed patients receiving citalopram, the reported incidence of decreased libido and anorgasmia was 1.3% (N=638 females) and 1.1% (N=252 females), respectively.

There are no adequately designed studies examining sexual dysfunction with citalopram treatment.

Priapism has been reported with all SSRIs.

While it is difficult to know the precise risk of sexual dysfunction associated with the use of SSRIs, physicians should routinely inquire about such possible side effects.

Vital Sign Changes

Citalopram and placebo groups were compared with respect to (1) mean change from baseline in vital signs (pulse, systolic blood pressure, and diastolic blood pressure) and (2) the incidence of patients meeting criteria for potentially clinically significant changes from baseline in these variables. These analyses did not reveal any clinically important changes in vital signs associated with citalopram treatment. In addition, a comparison of supine and standing vital sign measures for citalopram and placebo treatments indicated that citalopram treatment is not associated with orthostatic changes.

Weight Changes

Patients treated with citalopram in controlled trials experienced a weight loss of about 0.5 kg compared to no change for placebo patients.

Laboratory Changes

Citalopram and placebo groups were compared with respect to (1) mean change from baseline in various serum chemistry, hematology, and urinalysis variables, and (2) the incidence of patients meeting criteria for potentially clinically significant changes from baseline in these variables. These analyses revealed no clinically important changes in laboratory test parameters associated with citalopram treatment.

ECG Changes

In a thorough QT study, citalopram was found to be associated with a dose-dependent increase in the QTc interval (see WARNINGS: QT-Prolongation and Torsade de Pointes).

Electrocardiograms from citalopram (N=802) and placebo (N=241) groups were compared with respect to outliers defined as subjects with QTc changes over 60 msec from baseline or absolute values over 500 msec post-dose, and subjects with heart rate increases to over 100 bpm or decreases to less than 50 bpm with a 25% change from baseline (tachycardic or bradycardic outliers, respectively). In the citalopram group 1.9% of the patients had a change from baseline in QTcF >60 msec compared to 1.2% of the patients in the placebo group. None of the patients in the placebo group had a post-dose QTcF >500 msec compared to 0.5% of the patients in the citalopram group. The incidence of tachycardic outliers was 0.5% in the citalopram group and 0.4% in the placebo group. The incidence of bradycardic outliers was 0.9% in the citalopram group and 0.4% in the placebo group.

Other Events Observed During the Premarketing Evaluation of Citalopram

Following is a list of WHO terms that reflect treatment-emergent adverse events, as defined in the introduction to the ADVERSE REACTIONSsection, reported by patients treated with citalopram at multiple doses in a range of 10 to 80 mg/day during any phase of a trial within the premarketing database of 4,422 patients. All reported events are included except those already listed in TABLE 3 or elsewhere in labeling, those events for which a drug cause was remote, those event terms which were so general as to be uninformative, and those occurring in only one patient. It is important to emphasize that, although the events reported occurred during treatment with citalopram, they were not necessarily caused by it.

Events are further categorized by body system and listed in order of decreasing frequency according to the following definitions: frequent adverse events are those occurring on one or more occasions in at least 1/100 patients; infrequent adverse events are those occurring in less than 1/100 patients but at least 1/1,000 patients; rare events are those occurring in fewer than 1/1,000 patients.

Cardiovascular- Frequent:tachycardia, postural hypotension, hypotension. Infrequent:hypertension, bradycardia, edema (extremities), angina pectoris, extrasystoles, cardiac failure, flushing, myocardial infarction, cerebrovascular accident, myocardial ischemia. Rare:transient ischemic attack, phlebitis, atrial fibrillation, cardiac arrest, bundle branch block.

Central and Peripheral Nervous System Disorders- Frequent:paresthesia, migraine. Infrequent:hyperkinesia, vertigo, hypertonia, extrapyramidal disorder, leg cramps, involuntary muscle contractions, hypokinesia, neuralgia, dystonia, abnormal gait, hypesthesia, ataxia. Rare:abnormal coordination, hyperesthesia, ptosis, stupor.

Endocrine Disorders- Rare:hypothyroidism, goiter, gynecomastia.

Gastrointestinal Disorders- Frequent:saliva increased, flatulence. Infrequent:gastritis, gastroenteritis, stomatitis, eructation, hemorrhoids, dysphagia, teeth grinding, gingivitis, esophagitis. Rare:colitis, gastric ulcer, cholecystitis, cholelithiasis, duodenal ulcer, gastroesophageal reflux, glossitis, jaundice, diverticulitis, rectal hemorrhage, hiccups.

General- Infrequent:hot flushes, rigors, alcohol intolerance, syncope, influenza-like symptoms. Rare:hay fever.

Hemic and Lymphatic Disorders- Infrequent:purpura, anemia, epistaxis, leukocytosis, leucopenia, lymphadenopathy. Rare:pulmonary embolism, granulocytopenia, lymphocytosis, lymphopenia, hypochromic anemia, coagulation disorder, gingival bleeding.

Metabolic and Nutritional Disorders- Frequent:decreased weight, increased weight. Infrequent:increased hepatic enzymes, thirst, dry eyes, increased alkaline phosphatase, abnormal glucose tolerance. Rare:bilirubinemia, hypokalemia, obesity, hypoglycemia, hepatitis, dehydration.

Musculoskeletal System Disorders- Infrequent:arthritis, muscle weakness, skeletal pain. Rare:bursitis, osteoporosis.

Psychiatric Disorders- Frequent:impaired concentration, amnesia, apathy, depression, increased appetite, aggravated depression, suicide attempt, confusion. Infrequent:increased libido, aggressive reaction, paroniria, drug dependence, depersonalization, hallucination, euphoria, psychotic depression, delusion, paranoid reaction, emotional lability, panic reaction, psychosis. Rare:catatonic reaction, melancholia.

Reproductive Disorders/Female*- Frequent:amenorrhea. Infrequent:galactorrhea, breast pain, breast enlargement, vaginal hemorrhage.

*% based on female subjects only: 2,955

Respiratory System Disorders- Frequent:coughing. Infrequent:bronchitis, dyspnea, pneumonia. Rare:asthma, laryngitis, bronchospasm, pneumonitis, sputum increased.

Skin and Appendages Disorders- Frequent:rash, pruritus. Infrequent:photosensitivity reaction, urticaria, acne, skin discoloration, eczema, alopecia, dermatitis, skin dry, psoriasis. Rare:hypertrichosis, decreased sweating, melanosis, keratitis, cellulitis, pruritus ani.

Special Senses- Frequent:accommodation abnormal, taste perversion. Infrequent:tinnitus, conjunctivitis, eye pain. Rare:mydriasis, photophobia, diplopia, abnormal lacrimation, cataract, taste loss.

Urinary System Disorders- Frequent:polyuria. Infrequent:micturition frequency, urinary incontinence, urinary retention, dysuria. Rare:facial edema, hematuria, oliguria, pyelonephritis, renal calculus, renal pain.

Other Events Observed During the Postmarketing Evaluation of Citalopram

It is estimated that over 30 million patients have been treated with citalopram since market introduction. Although no causal relationship to citalopram treatment has been found, the following adverse events have been reported to be temporally associated with citalopram treatment, and have not been described elsewhere in labeling: acute renal failure, akathisia, allergic reaction, anaphylaxis, angioedema, choreoathetosis, chest pain, delirium, dyskinesia, ecchymosis, epidermal necrolysis, erythema multiforme, gastrointestinal hemorrhage, angle-closure glaucoma, grand mal convulsions, hemolytic anemia, hepatic necrosis, myoclonus, nystagmus, pancreatitis, priapism, prolactinemia, prothrombin decreased, QT prolonged, rhabdomyolysis, spontaneous abortion, thrombocytopenia, thrombosis, ventricular arrhythmia, torsade de pointes, withdrawal syndrome, anosmia, and hyposmia.

DRUG ABUSE AND DEPENDENCE

Controlled Substance Class

Citalopram is not a controlled substance.

Physical and Psychological Dependence

Animal studies suggest that the abuse liability of citalopram is low. Citalopram has not been systematically studied in humans for its potential for abuse, tolerance, or physical dependence. The premarketing clinical experience with citalopram did not reveal any drug-seeking behavior. However, these observations were not systematic and it is not possible to predict, on the basis of this limited experience, the extent to which a CNS-active drug will be misused, diverted, and/or abused once marketed. Consequently, physicians should carefully evaluate citalopram patients for history of drug abuse and follow such patients closely, observing them for signs of misuse or abuse (e.g., development of tolerance, incrementations of dose, drug-seeking behavior).

OVERDOSAGE

Human Experience

In clinical trials of citalopram, there were reports of citalopram overdose, including overdoses of up to 2,000 mg, with no associated fatalities. During the postmarketing evaluation of citalopram, citalopram overdoses, including overdoses of up to 6,000 mg, have been reported. As with other SSRI's, a fatal outcome in a patient who has taken an overdose of citalopram has been rarely reported.

Symptoms most often accompanying citalopram overdose, alone or in combination with other drugs and/or alcohol, included dizziness, sweating, nausea, vomiting, tremor, somnolence, and sinus tachycardia. In more rare cases, observed symptoms included amnesia, confusion, coma, convulsions, hyperventilation, cyanosis, rhabdomyolysis, and ECG changes (including QTc prolongation, nodal rhythm, ventricular arrhythmia, and very rare cases of torsade de pointes). Acute renal failure has been very rarely reported accompanying overdose.

Management of Overdose

Establish and maintain an airway to ensure adequate ventilation and oxygenation. Gastric evacuation by lavage and use of activated charcoal should be considered. Careful observation and cardiac and vital sign monitoring are recommended, along with general symptomatic and supportive care. Due to the large volume of distribution of citalopram, forced diuresis, dialysis, hemoperfusion, and exchange transfusion are unlikely to be of benefit. There are no specific antidotes for citalopram.

In managing overdosage, consider the possibility of multiple-drug involvement. The physician should consider contacting a poison control center for additional information on the treatment of any overdose.

DOSAGE AND ADMINISTRATION

Citalopram Oral Solution should be administered once daily, in the morning or evening, with or without food.

Initial Treatment

Citalopram Oral Solution should be administered at an initial dose of 20 mg once daily, with an increase to a maximum dose of 40 mg/day at an interval of no less than one week. Doses above 40 mg/day are not recommended due to the risk of QT prolongation. Additionally, the only study pertinent to dose response for effectiveness did not demonstrate an advantage for the 60 mg/day dose over the 40 mg/day dose.

Special Populations

20 mg/day is the maximum recommended dose for patients who are greater than 60 years of age, patients with hepatic impairment, and for CYP2C19 poor metabolizers or those patients taking cimetidine or another CYP2C19 inhibitor (see WARNINGS).

No dosage adjustment is necessary for patients with mild or moderate renal impairment. Citalopram Oral Solution should be used with caution in patients with severe renal impairment.

Treatment of Pregnant Women During the Third Trimester

Neonates exposed to Citalopram Oral Solution and other SSRIs or SNRIs, late in the third trimester, have developed complications requiring prolonged hospitalization, respiratory support, and tube feeding (see PRECAUTIONS). When treating pregnant women with Citalopram Oral Solution during the third trimester, the physician should carefully consider the potential risks and benefits of treatment.

Maintenance Treatment

It is generally agreed that acute episodes of depression require several months or longer of sustained pharmacologic therapy. Systematic evaluation of Citalopram Oral Solution in two studies has shown that its antidepressant efficacy is maintained for periods of up to 24 weeks following 6 or 8 weeks of initial treatment (32 weeks total). In one study, patients were assigned randomly to placebo or to the same dose of Citalopram Oral Solution (20 to 60 mg/day) during maintenance treatment as they had received during the acute stabilization phase, while in the other study, patients were assigned randomly to continuation of Citalopram Oral Solution 20 or 40 mg/day, or placebo, for maintenance treatment. In the latter study, the rates of relapse to depression were similar for the two dose groups (see CLINICAL PHARMACOLOGY; Clinical Efficacy Trials). Based on these limited data, it is not known whether the dose of citalopram needed to maintain euthymia is identical to the dose needed to induce remission. If adverse reactions are bothersome, a decrease in dose to 20 mg/day can be considered.

Discontinuation of Treatment with Citalopram Oral Solution

Symptoms associated with discontinuation of Citalopram Oral Solution and other SSRIs and SNRIs have been reported (see PRECAUTIONS). Patients should be monitored for these symptoms when discontinuing treatment. A gradual reduction in the dose rather than abrupt cessation is recommended whenever possible. If intolerable symptoms occur following a decrease in the dose or upon discontinuation of treatment, then resuming the previously prescribed dose may be considered. Subsequently, the physician may continue decreasing the dose but at a more gradual rate.

Switching Patients To or From a Monoamine Oxidase Inhibitor (MAOI) Intended to Treat Psychiatric Disorders

At least 14 days should elapse between discontinuation of an MAOI intended to treat psychiatric disorders and initiation of therapy with Citalopram Oral Solution. Conversely, at least 14 days should be allowed after stopping Citalopram Oral Solution before starting an MAOI intended to treat psychiatric disorders (see CONTRAINDICATIONS).

Use of Citalopram Oral Solution with Other MAOIs, Such as Linezolid or Methylene Blue

Do not start Citalopram Oral Solution in a patient who is being treated with linezolid or intravenous methylene blue because there is an increased risk of serotonin syndrome. In a patient who requires more urgent treatment of a psychiatric condition, other interventions, including hospitalization, should be considered (see CONTRAINDICATIONS).

In some cases, a patient already receiving Citalopram Oral Solution therapy may require urgent treatment with linezolid or intravenous methylene blue. If acceptable alternatives to linezolid or intravenous methylene blue treatment are not available and the potential benefits of linezolid or intravenous methylene blue treatment are judged to outweigh the risks of serotonin syndrome in a particular patient, Citalopram Oral Solution should be stopped promptly, and linezolid or intravenous methylene blue can be administered. The patient should be monitored for symptoms of serotonin syndrome for 2 weeks or until 24 hours after the last dose of linezolid or intravenous methylene blue, whichever comes first. Therapy with Citalopram Oral Solution may be resumed 24 hours after the last dose of linezolid or intravenous methylene blue (see WARNINGS).

The risk of administering methylene blue by non-intravenous routes (such as oral tablets or by local injection) or in intravenous doses much lower than 1 mg/kg with Citalopram Oral Solution is unclear. The clinician should, nevertheless, be aware of the possibility of emergent symptoms of serotonin syndrome with such use (see WARNINGS).

HOW SUPPLIED

Citalopram Oral Solution, USP

10 mg/5 mL, clear, colorless, peppermint flavored solution - (473 mL (16 fl oz)) NDC 62135-540-47

10 mL Unit-Dose Cup NDC 62135-540-10

20 Unit-Dose Cups of 10 mL each NDC 62135-540-24

Storage

Store at 20° to 25°C (68° to 77°F); excursions permitted to 15° to 30°C (59° to 86°F). [see USP Controlled Room Temperature]

ANIMAL TOXICOLOGY

Retinal Changes in Rats

Pathologic changes (degeneration/atrophy) were observed in the retinas of albino rats in the 2-year carcinogenicity study with citalopram. There was an increase in both incidence and severity of retinal pathology in both male and female rats receiving 80 mg/kg/day (13 times the maximum recommended daily human dose of 60 mg on a mg/m^2basis). Similar findings were not present in rats receiving 24 mg/kg/day for two years, in mice treated for 18 months at doses up to 240 mg/kg/day or in dogs treated for one year at doses up to 20 mg/kg/day (4, 20 and 10 times, respectively, the maximum recommended daily human dose on a mg/m^2basis).

Additional studies to investigate the mechanism for this pathology have not been performed, and the potential significance of this effect in humans has not been established.

Cardiovascular Changes in Dogs

In a one-year toxicology study, 5 of 10 beagle dogs receiving oral doses of 8 mg/kg/day (4 times the maximum recommended daily human dose of 60 mg on a mg/m^2basis) died suddenly between weeks 17 and 31 following initiation of treatment. Although appropriate data from that study are not available to directly compare plasma levels of citalopram (CT) and its metabolites, demethylcitalopram (DCT) and didemethylcitalopram (DDCT), to levels that have been achieved in humans, pharmacokinetic data indicate that the relative dog-to-human exposure was greater for the metabolites than for citalopram. Sudden deaths were not observed in rats at doses up to 120 mg/kg/day, which produced plasma levels of CT, DCT and DDCT similar to those observed in dogs at doses of 8 mg/kg/day. A subsequent intravenous dosing study demonstrated that in beagle dogs, DDCT caused QT prolongation, a known risk factor for the observed outcome in dogs. This effect occurred in dogs at doses producing peak DDCT plasma levels of 810 to 3,250 nM (39 to 155 times the mean steady state DDCT plasma level measured at the maximum recommended human daily dose of 60 mg). In dogs, peak DDCT plasma concentrations are approximately equal to peak CT plasma concentrations, whereas in humans, steady state DDCT plasma concentrations are less than 10% of steady state CT plasma concentrations. Assays of DDCT plasma concentrations in 2,020 citalopram-treated individuals demonstrated that DDCT levels rarely exceeded 70 nM; the highest measured level of DDCT in human overdose was 138 nM. While DDCT is ordinarily present in humans at lower levels than in dogs, it is unknown whether there are individuals who may achieve higher DDCT levels. The possibility that DCT, a principal metabolite in humans, may prolong the QT interval in dogs has not been directly examined because DCT is rapidly converted to DDCT in that species.

Manufactured for:
Chartwell RX, LLC
Congers, NY 10920

L71060

Rev. 01/2026

Medication Guide

Citalopram (sye tal’ oh pram)

Oral Solution, USP

Rx Only

Read the Medication Guide that comes with Citalopram Oral Solution before you start taking it and each time you get a refill. There may be new information. This Medication Guide does not take the place of talking to your healthcare provider about your medical condition or treatment. Talk with your healthcare provider if there is something you do not understand or want to learn more about.

What is the most important information I should know about Citalopram Oral Solution?

Citalopram Oral Solution and other antidepressant medicines may cause serious side effects, including:

1. Suicidal thoughts or actions:

- Citalopram Oral Solution and other antidepressant medicines may increase suicidal thoughts or actionsin some children, teenagers, or young adults within the first few months of treatment or when the dose is changed.
- Depression or other serious mental illnesses are the most important causes of suicidal thoughts or actions.
- Watch for these changes and call your healthcare provider right away if you notice:
  - New or sudden changes in mood, behavior, actions, thoughts, or feelings, especially if severe.
  - Pay particular attention to such changes when Citalopram Oral Solution is started or when the dose is changed.

Keep all follow-up visits with your healthcare provider and call between visits if you are worried about symptoms.

Call your healthcare provider right away if you have any of the following symptoms, or call 911 if an emergency, especially if they are new, worse, or worry you:

- attempts to commit suicide
- acting on dangerous impulses
- acting aggressive or violent
- thoughts about suicide or dying
- new or worse depression
- new or worse anxiety or panic attacks
- feeling agitated, restless, angry or irritable
- trouble sleeping
- an increase in activity or talking more than what is normal for you
- other unusual changes in behavior or mood

Call your healthcare provider right away if you have any of the following symptoms, or call 911 if an emergency. Citalopram Oral Solution may be associated with these serious side effects.

2. Changes in the electrical activity of your heart (QT prolongation and Torsade de Pointes).

This condition can be life threatening. The symptoms may include:

- chest pain
- fast or slow heartbeat
- shortness of breath
- dizziness or fainting

3. Serotonin Syndrome. This condition can be life-threatening and may include:

- agitation, hallucinations, coma or other changes in mental status
- coordination problems or muscle twitching (overactive reflexes)
- racing heartbeat, high or low blood pressure
- sweating or fever
- nausea, vomiting, or diarrhea
- muscle rigidity

4. Severe allergic reactions:

- trouble breathing
- swelling of the face, tongue, eyes or mouth
- rash, itchy welts (hives) or blisters, alone or with fever or joint pain

5. Abnormal Bleeding:Citalopram Oral Solution and other antidepressant medicines may increase your risk of bleeding or bruising, especially if you take the blood thinner warfarin (Coumadin®, Jantoven®), a non-steroidal anti-inflammatory drug (NSAIDs, like ibuprofen or naproxen), or aspirin.

6. Seizures or convulsions.

7. Manic episodes:

- greatly increased energy
- severe trouble sleeping
- racing thoughts
- reckless behavior
- unusually grand ideas
- excessive happiness or irritability
- talking more or faster than usual

8. Changes in appetite or weight. Children and adolescents should have height and weight monitored during treatment.

9. Low salt (sodium) levels in the blood. Elderly people may be at greater risk for this. Symptoms may include:

- headache
- weakness or feeling unsteady
- confusion, problems concentrating or thinking or memory problems

10. Visual problems.

- eye pain
- changes in vision
- swelling or redness in or around the eye

Only some people are at risk for these problems. You may want to undergo an eye examination to see if you are at risk and receive preventative treatment if you are.

11. Sexual problems (dysfunction).Taking serotonin and norepinephrine reuptake inhibitors (SSRIs), including citalopram, may cause sexual problems.

Symptoms in males may include:

- Delayed ejaculation or inability to have an ejaculation
- Decreased sex drive
- Problems getting or keeping an erection

Symptoms in females may include:

- Decreased sex drive
- Delayed orgasm or inability to have an orgasm

Talk to your healthcare provider if you develop any changes in your sexual function or if you have any questions or concerns about sexual problems during treatment with citalopram. There may be treatments your healthcare provider can suggest.

Do not stop Citalopram Oral Solution without first talking to your healthcare provider.

Stopping Citalopram Oral Solution too quickly may cause serious symptoms including:

- anxiety, irritability, high or low mood, feeling restless or changes in sleep habits
- headache, sweating, nausea, dizziness
- electric shock-like sensations, shaking, confusion

What is Citalopram Oral Solution?

Citalopram Oral Solution is a prescription medicine used to treat depression. It is important to talk with your healthcare provider about the risks of treating depression and also the risks of not treating it. You should discuss all treatment choices with your healthcare provider. Citalopram Oral Solution is also used to treat:

- Major Depressive Disorder (MDD)

Talk to your healthcare provider if you do not think that your condition is getting better with Citalopram Oral Solution treatment.

Who should not take Citalopram Oral Solution?

Do not take Citalopram Oral Solution if you:

- are allergic to citalopram hydrobromide or escitalopram oxalate or any of the ingredients in Citalopram Oral Solution. See the end of this Medication Guide for a complete list of ingredients in Citalopram Oral Solution.
- if you take a Monoamine Oxidase Inhibitor (MAOI). Ask your healthcare provider or pharmacist if you are not sure if you take an MAOI, including the antibiotic linezolid.
- Do not take an MAOI within 2 weeks of stopping Citalopram Oral Solution unless directed to do so by your physician.
- Do not start Citalopram Oral Solution if you stopped taking an MAOI in the last 2 weeks unless directed to do so by your physician.

People who take Citalopram Oral Solution close in time to an MAOI may have serious or even life-threatening side effects. Get medical help right away if you have any of these symptoms:

- high fever
- uncontrolled muscle spasms
- stiff muscles
- rapid changes in heart rate or blood pressure
- confusion
- loss of consciousness (pass out)
- take the antipsychotic medicine pimozide (Orap®) because this can cause serious heart problems.
- have a heart problem including congenital long QT syndrome.

What should I tell my healthcare provider before taking Citalopram Oral Solution? Ask if you are not sure.

Before starting Citalopram Oral Solution, tell your healthcare provider if you:

- Are taking certain drugs such as:
  - Amphetamines
  - Medicines for heart problems
  - Medicines that lower your potassium or magnesium levels in your body
  - Cimetidine
  - Triptans used to treat migraine headache
  - Medicines used to treat mood, anxiety, psychotic or thought disorders, including tricyclics, lithium, SSRIs, SNRIs, or antipsychotics
  - Tramadol, Meperidine, Methadone, or other opioids
  - Over-the-counter supplements such as tryptophan or St. John's Wort
- have liver problems
- have kidney problems
- have heart problems
- have or had seizures or convulsions
- have bipolar disorder or mania
- have low sodium levels in your blood
- have a history of a stroke
- have high blood pressure
- have or had bleeding problems
- are pregnant or plan to become pregnant. It is not known if Citalopram Oral Solution will harm your unborn baby. Talk to your healthcare provider about the benefits and risks of treating depression during pregnancy
- are breast-feeding or plan to breastfeed. Some citalopram may pass into your breast milk. Talk to your healthcare provider about the best way to feed your baby while taking Citalopram Oral Solution.

Tell your healthcare provider about all the medicines that you take, including prescription and non-prescription medicines, vitamins, and herbal supplements. Citalopram Oral Solution and some medicines may interact with each other, may not work as well, or may cause serious side effects.

Your healthcare provider or pharmacist can tell you if it is safe to take Citalopram Oral Solution with your other medicines. Do not start or stop any medicine while taking Citalopram Oral Solution without talking to your healthcare provider first.

If you take Citalopram Oral Solution, you should not take any other medicines that contain citalopram hydrobromide or escitalopram oxalate including: Lexapro.

How should I take Citalopram Oral Solution?

- Take Citalopram Oral Solution exactly as prescribed. Your healthcare provider may need to change the dose of Citalopram Oral Solution until it is the right dose for you.
- Citalopram Oral Solution may be taken with or without food.
- If you miss a dose of Citalopram Oral Solution, take the missed dose as soon as you remember. If it is almost time for the next dose, skip the missed dose and take your next dose at the regular time. Do not take two doses of Citalopram Oral Solution at the same time.
- If you take too much Citalopram Oral Solution, call your healthcare provider or poison control center right away, or get emergency treatment.

What should I avoid while taking Citalopram Oral Solution?

Citalopram Oral Solution can cause sleepiness or may affect your ability to make decisions, think clearly, or react quickly. You should not drive, operate heavy machinery, or do other dangerous activities until you know how Citalopram Oral Solution affects you. Do not drink alcohol while using Citalopram Oral Solution.

What are the possible side effects of Citalopram Oral Solution?

Citalopram Oral Solution may cause serious side effects, including:

See "What is the most important information I should know about Citalopram Oral Solution?"

Common possible side effects in people who take Citalopram Oral Solution include:

- Nausea
- Sleepiness
- Weakness
- Dizziness
- Feeling anxious
- Trouble sleeping
- Sexual problems
- Sweating
- Shaking
- Not feeling hungry
- Dry mouth
- Constipation
- Diarrhea
- Respiratory Infections
- Yawning

Other side effects in children and adolescents include:

- increased thirst
- abnormal increase in muscle movement or agitation
- nose bleed
- urinating more often
- heavy menstrual periods
- possible slowed growth rate and weight change. Your child's height and weight should be monitored during treatment with Citalopram Oral Solution.

Tell your healthcare provider if you have any side effect that bothers you or that does not go away. These are not all the possible side effects of Citalopram Oral Solution. For more information, ask your healthcare provider or pharmacist.

CALL YOUR DOCTOR FOR MEDICAL ADVICE ABOUT SIDE EFFECTS. YOU MAY REPORT SIDE EFFECTS TO THE FDA AT 1-800-FDA-1088.

How should I store Citalopram Oral Solution?

• Store Citalopram Oral Solution at 25°C (77°F), between 15°C to 30°C (59°F to 86°F).

• Keep Citalopram Oral Solution bottle closed tightly.

Keep Citalopram Oral Solution and all medicines out of the reach of children.

General information about Citalopram Oral Solution

Medicines are sometimes prescribed for purposes other than those listed in the Medication Guide. Do not use Citalopram Oral Solution for a condition for which it was not prescribed. Do not give Citalopram Oral Solution to other people, even if they have the same condition. It may harm them.

This Medication Guide summarizes the most important information about Citalopram Oral Solution. If you would like more information, talk with your healthcare provider. You may ask your healthcare provider or pharmacist for information about Citalopram Oral Solution that is written for healthcare professionals.

For more information about Citalopram Oral Solution call 1-845-232-1683.

What are the ingredients in Citalopram Oral Solution?

Active ingredient: citalopram hydrobromide

Inactive ingredients: sorbitol, purified water, propylene glycol, methylparaben, peppermint flavor, propylparaben.

This Medication Guide has been approved by the U.S. Food and Drug Administration.

Trademarks are the property of their respective owners.

Manufactured for:
Chartwell RX, LLC
Congers, NY 10920

L71061

Rev. 01/2026

PACKAGE LABEL-PRINCIPAL DISPLAY PANEL

Citalopram Oral Solution, USP 10 mg/5 mL - NDC 62135-540-47 - 473 mL Bottle Label

Citalopram Oral Solution, USP 20 mg/10 mL - NDC 62135-540-10 - 10 mL Unit-Dose Cup Label